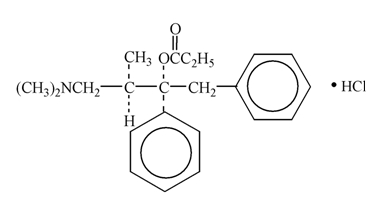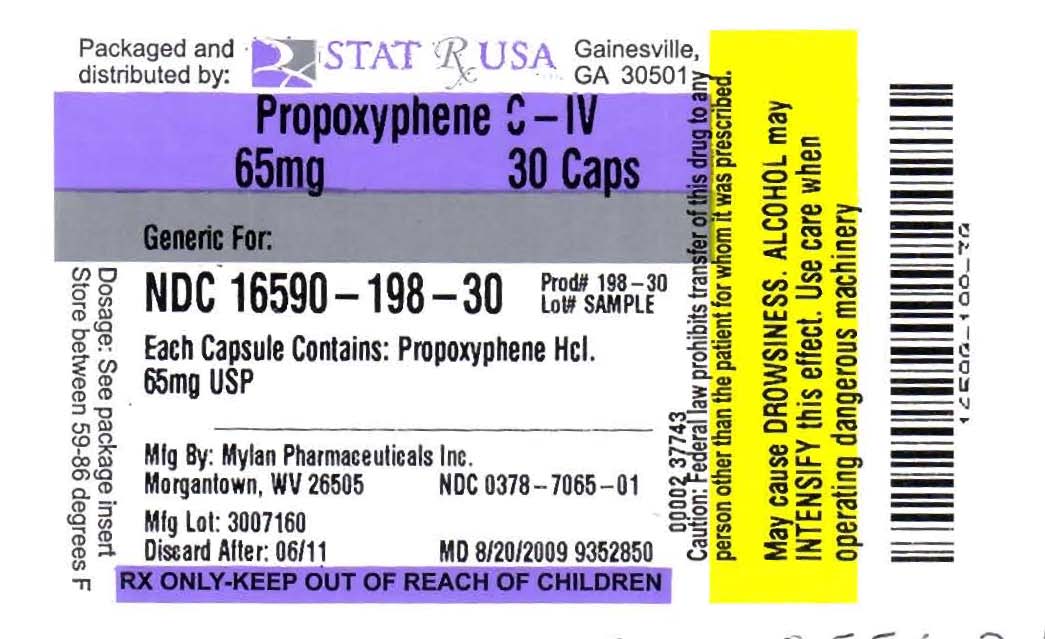 DRUG LABEL: Propoxyphene
NDC: 16590-198 | Form: CAPSULE
Manufacturer: Stat Rx USA
Category: prescription | Type: HUMAN PRESCRIPTION DRUG LABEL
Date: 20091027
DEA Schedule: CIV

ACTIVE INGREDIENTS: PROPOXYPHENE HYDROCHLORIDE  65 mg/1 1

Insert

DESCRIPTION

Propoxyphene hydrochloride, USP is an odorless, white crystalline powder with a bitter taste. It is freely soluble in water. Chemically, it is (2S,3R)-(+)-4-(Dimethylamino)-3-methyl-1,2-diphenyl-2-butanol propionate (ester) hydrochloride, which can be represented by the accompanying structural formula. Its molecular formula is C22H29NO2∙HCl and its molecular weight is 375.93.

Each capsule contains 65 mg (172.9 μmol) propoxyphene hydrochloride. It also contains the following inactive ingredients: anhydrous lactose, magnesium stearate, microcrystalline cellulose, pregelatinized starch and sodium lauryl sulfate. The empty hard-shell hypromellose capsule shells contain carnauba wax, carrageenan, hypromellose, potassium chloride, synthetic red iron oxide and titanium dioxide. In addition, the imprinting ink contains black iron oxide, potassium hydroxide, propylene glycol, shellac and strong ammonia solution.

CLINICAL PHARMACOLOGYPharmacology

Propoxyphene is a centrally acting opiate analgesic. In vitro studies demonstrated propoxyphene and the metabolite norpropoxyphene inhibit sodium channels (local anesthetic effect) with norpropoxyphene being approximately 2-fold more potent than propoxyphene and propoxyphene approximately 10-fold more potent than lidocaine. Propoxyphene and norpropoxyphene inhibit the voltage-gated potassium current carried by cardiac rapidly activating delayed rectifier (hERG) channels with approximately equal potency. It is unclear if the effects on ion channels occur within therapeutic dose range.

Pharmacokinetics Absorption

Peak plasma concentrations of propoxyphene are reached in 2 to 2.5 hours. After a 65 mg oral dose of propoxyphene hydrochloride, peak plasma levels of 0.05 to 0.1 mcg/mL for propoxyphene and 0.1 to 0.2 mcg /mL for norpropoxyphene (major metabolite) are achieved. Repeated doses of propoxyphene at 6 hour intervals lead to increasing plasma concentrations, with a plateau after the ninth dose at 48 hours. Propoxyphene has a half-life of 6 to 12 hours, whereas that of norpropoxyphene is 30 to 36 hours.

Distribution

Propoxyphene is about 80% bound to proteins and has a large volume of distribution, 16 L/kg.

Metabolism

Propoxyphene undergoes extensive first-pass metabolism by intestinal and hepatic enzymes. The major route of metabolism is cytochrome CYP3A4 mediated N-demethylation to norpropoxyphene, which is excreted by the kidneys. Ring hydroxylation and glucuronide formation are minor metabolic pathways.

Excretion

In 48 hours, approximately 20% to 25% of the administered dose of propoxyphene is excreted via the urine, most of which is free or conjugated norpropoxyphene. The renal clearance rate of propoxyphene is 2.6 L/min.

Special Populations Geriatric Patients

After oral administration of propoxyphene in elderly patients (70 to 78 years), much longer half-lives of propoxyphene and norpropoxyphene have been reported (propropoxyphene 13 to 35 hours, norpropoxyphene 22 to 41 hours). In addition, the AUC was an average of 3-fold higher and the Cmax was an average of 2.5-fold higher in the elderly when compared to a younger (20 to 28 years) population. Longer dosage intervals may be considered in the elderly because the metabolism of propoxyphene may be reduced in this patient population. After multiple oral doses of propoxyphene in elderly patients (70 to 78 years), the Cmax of the metabolite (norpropoxyphene) was increased 5-fold.

Pediatric Patients

Propoxyphene has not been studied in pediatric patients.

Hepatic Impairment

No formal pharmacokinetic study of propoxyphene has been conducted in patients with mild, moderate or severe hepatic impairment.

After oral administration of propoxyphene in patients with cirrhosis, plasma concentrations of propoxyphene were considerably higher and norpropoxyphene concentrations were much lower than in control patients. This is presumably because of a decreased first-pass metabolism of orally administered propoxyphene in these patients. The AUC ratio of norpropoxyphene: propoxyphene was significantly lower in patients with cirrhosis (0.5 to 0.9) than in controls (2.5 to 4).

Renal Impairment

No formal pharmacokinetic study of propoxyphene has been conducted in patients with mild, moderate or severe renal impairment.

After oral administration of propoxyphene in anephric patients, the AUC and Cmax values were an average of 76% and 88% greater, respectively. Dialysis removes only insignificant amounts (8%) of administered dose of propoxyphene.

Drug Interactions

The metabolism of propoxyphene may be altered by strong CYP3A4 inhibitors (such as ritonavir, ketoconazole, itraconazole, troleandomycin, clarithromycin, nelfinavir, nefazadone, amiodarone, amprenavir, aprepitant, diltiazem, erythromycin, fluconazole, fosamprenavir, grapefruit juice and verapamil) leading to enhanced propoxyphene plasma levels. On the other hand, strong CYP3A4 inducers such as rifampin may lead to enhanced metabolite (norpropoxyphene) levels.

Propoxyphene is also thought to possess CYP3A4 and CYP2D6 enzyme inhibiting properties. Coadministration with a drug that is a substrate of CYP3A4 or CYP2D6, may result in higher plasma concentrations and increased pharmacologic or adverse effects of that drug.

INDICATIONS AND USAGE

INDICATION

Propoxyphene hydrochloride capsules are indicated for the relief of mild to moderate pain.

CONTRAINDICATIONS

Propoxyphene hydrochloride capsules are contraindicated in patients with known hypersensitivity to propoxyphene.

Propoxyphene hydrochloride capsules are contraindicated in patients with significant respiratory depression (in unmonitored settings or the absence of resuscitative equipment) and patients with acute or severe asthma or hypercarbia.

Propoxyphene hydrochloride capsules are contraindicated in any patient who has or is suspected of having paralytic ileus.

WARNINGS

WARNINGSRisk of Overdose

There have been numerous cases of accidental and intentional overdose with propoxyphene products either alone or in combination with other CNS depressants, including alcohol. Fatalities within the first hour of overdosage are not uncommon. Many of the propoxyphene-related deaths have occurred in patients with previous histories of emotional disturbances or suicidal ideation/attempts and/or concomitant administration of sedatives, tranquilizers, muscle relaxants, antidepressants or other CNS-depressant drugs. Do not prescribe propoxyphene for patients who are suicidal or have a history of suicidal ideation.

Respiratory Depression

Respiratory depression is the chief hazard from all opioid agonist preparations. Respiratory depression occurs most frequently in elderly or debilitated patients, usually following large initial doses in non-tolerant patients, or when opioids are given in conjunction with other agents that depress respiration. Propoxyphene should be used with extreme caution in patients with significant chronic obstructive pulmonary disease or cor pulmonale, and in patients having substantially decreased respiratory reserve, hypoxia, hypercapnia, or preexisting respiratory depression. In such patients, even usual therapeutic doses of propoxyphene may decrease respiratory drive to the point of apnea. In these patients alternative non-opioid analgesics should be considered and opioids should be employed only under careful medical supervision at the lowest effective dose.

Hypotensive Effect

Propoxyphene, like all opioid analgesics, may cause severe hypotension in an individual whose ability to maintain blood pressure has been compromised by a depleted blood volume, or after concurrent administration with drugs such as phenothiazines or other agents which compromise vasomotor tone. Propoxyphene may produce orthostatic hypotension in ambulatory patients. Propoxyphene, like all opioid analgesics, should be administered with caution to patients in circulatory shock, since vasodilatation produced by the drug may further reduce cardiac output and blood pressure.

Head Injury and Increased Intracranial Pressure

The respiratory depressant effects of narcotics and their capacity to elevate cerebrospinal fluid pressure may be markedly exaggerated in the presence of head injury, other intracranial lesions or a preexisting increase in intracranial pressure. Furthermore, narcotics produce adverse reactions which may obscure the clinical course of patients with head injuries.

Drug Interactions

The concomitant use of propoxyphene and CNS depressants, including alcohol, can result in potentially serious adverse events including death. Because of its added depressant effects, propoxyphene should be prescribed with caution for those patients whose medical condition requires the concomitant administration of sedatives, tranquilizers, muscle relaxants, antidepressants or other CNS-depressant drugs.

Usage in Ambulatory Patients

Propoxyphene may impair the mental and/or physical abilities required for the performance of potentially hazardous tasks, such as driving a car or operating machinery. The patient should be cautioned accordingly.

Use with Alcohol

Patients should be cautioned about the concomitant use of propoxyphene products and alcohol because of potentially serious CNS-additive effects of these agents that can lead to death.

PRECAUTIONS

PRECAUTIONSTolerance and Physical Dependence

Tolerance is the need for increasing doses of opioids to maintain a defined effect such as analgesia (in the absence of disease progression or other external factors). Physical dependence is manifested by withdrawal symptoms after abrupt discontinuation of a drug or upon administration of an antagonist. Physical dependence and tolerance are not unusual during chronic opioid therapy.

The opioid abstinence or withdrawal syndrome is characterized by some or all of the following: restlessness, lacrimation, rhinorrhea, yawning, perspiration, chills, myalgia and mydriasis. Other symptoms also may develop, including: irritability, anxiety, backache, joint pain, weakness, abdominal cramps, insomnia, nausea, anorexia, vomiting, diarrhea, or increased blood pressure, respiratory rate or heart rate. In general, opioids should not be abruptly discontinued (see DOSAGE AND ADMINISTRATION: Cessation of Therapy).

If propoxyphene is abruptly discontinued in a physically dependent patient, an abstinence syndrome may occur (see DRUG ABUSE AND DEPENDENCE). If signs and symptoms of withdrawal occur, patients should be treated by reinstitution of opioid therapy followed by gradual tapered dose reduction of propoxyphene combined with symptomatic support (see DOSAGE AND ADMINISTRATION: Cessation of Therapy).

Use in Pancreatic/Biliary Tract Disease

Propoxyphene may cause spasm of the sphincter of Oddi and should be used with caution in patients with biliary tract disease, including acute pancreatitis. Opioids like propoxyphene may cause increases in the serum amylase level.

Hepatic or Renal Impairment

Insufficient information exists to make appropriate dosing recommendations regarding the use of either propoxyphene in patients with hepatic or renal impairment as a function of degree of impairment. Higher plasma concentrations and/or delayed elimination may occur in case of impaired hepatic function and/or impaired renal function (see CLINICAL PHARMACOLOGY).

If the drug is used in these patients, it should be used with caution because of the hepatic metabolism and renal excretion of propoxyphene metabolites.

Information for Patients/Caregivers

1. Patients should be advised to report pain and adverse experiences occurring during therapy. Individualization of dosage is essential to make optimal use of this medication.
2. Patients should be advised not to adjust the dose of propoxyphene without consulting the prescribing professional.
3. Patients should be advised that propoxyphene may impair mental and/or physical ability required for the performance of potentially hazardous tasks (e.g., driving, operating heavy machinery).
4. Patients should not combine propoxyphene with central nervous system depressants (e.g., sleep aids, tranquilizers) except by the orders of the prescribing physician, because additive effects may occur.
5. Patients should be instructed not to consume alcoholic beverages, including prescription and over-the-counter medications that contain alcohol, while using propoxyphene because of risk of serious adverse events including death.
6. Women of childbearing potential who become, or are planning to become, pregnant should be advised to consult their physician regarding the effects of analgesics and other drug use during pregnancy on themselves and their unborn child.
7. Patients should be advised that propoxyphene is a potential drug of abuse. They should protect it from theft, and it should never be given to anyone other than the individual for whom it was prescribed.
8. Patients should be advised that if they have been receiving treatment with propoxyphene for more than a few weeks and cessation of therapy is indicated, it may be appropriate to taper the propoxyphene dose, rather than abruptly discontinue it, due to the risk of precipitating withdrawal symptoms. Their physician can provide a dose schedule to accomplish a gradual discontinuation of the medication.

Drug Interactions with Propoxyphene

Propoxyphene is metabolized mainly via the human cytochrome P450 3A4 isoenzyme system (CYP3A4), therefore potential interactions may occur when propoxyphene is administered concurrently with agents that affect CYP3A4 activity.

The metabolism of propoxyphene may be altered by strong CYP3A4 inhibitors (such as ritonavir, ketoconazole, itraconazole, troleandomycin, clarithromycin, nelfinavir, nefazadone, amiodarone, amprenavir, aprepitant, diltiazem, erythromycin, fluconazole, fosamprenavir, grapefruit juice and verapamil) leading to enhanced propoxyphene plasma levels. Coadministration with agents that induce CYP3A4 activity may reduce the efficacy of propoxyphene. Strong CYP3A4 inducers such as rifampin may lead to enhanced metabolite (norpropoxyphene) levels.

Propoxyphene is also thought to possess CYP3A4 and CYP2D6 enzyme inhibiting properties and coadministration with drugs that rely on either of these enzymes for metabolism may result in increased pharmacologic or adverse effects of that drug. Severe neurologic signs, including coma, have occurred with concurrent use of carbamazepine (metabolized by CYP3A4).

Increased risk of bleeding has been observed with warfarin-like agents when given along with propoxyphene; however, the mechanistic basis of this interaction is unknown.

CNS Depressants

Patients receiving narcotic analgesics, general anesthetics, phenothiazines, other tranquilizers, sedative-hypnotics or other CNS depressants (including alcohol) concomitantly with propoxyphene may exhibit an additive CNS depression. Interactive effects resulting in respiratory depression, hypotension, profound sedation or coma may result if these drugs are taken in combination with the usual dosage of propoxyphene. When such combined therapy is contemplated, the dose of one or both agents should be reduced.

Mixed Agonist/Antagonist Opioid Analgesics

Agonist/antagonist analgesics (i.e., pentazocine, nalbuphine, butorphanol and buprenorphine) should be administered with caution to patients who have received or are receiving a course of therapy with a pure opioid agonist analgesic such as propoxyphene. In this situation, mixed agonist/antagonist analgesics may reduce the analgesic effect of propoxyphene and/or may precipitate withdrawal symptoms in these patients.

Monoamine Oxidase Inhibitors (MAOIs)

MAOIs have been reported to intensify the effects of at least one opioid drug causing anxiety, confusion and significant depression of respiration or coma. The use of propoxyphene is not recommended for patients taking MAOIs or within 14 days of stopping such treatment.

Carcinogenesis, Mutagenesis, Impairment of Fertility

The mutagenic and carcinogenic potential of propoxyphene has not been evaluated.

In animal studies there was no effect of propoxyphene on mating behavior, fertility, duration of gestation or parturition when rats were fed propoxyphene as a component of their daily diet at estimated daily propoxyphene intake up to 8-fold greater than the maximum human equivalent dose (HED) based on body surface area comparison. At this highest dose, fetal weight and survival on postnatal day 4 was reduced

Pregnancy Risk Summary Pregnancy Category C

There are no adequate and well controlled studies of propoxyphene in pregnant women. While there are limited data in the published literature, adequate animal reproduction studies have not been conducted with propoxyphene. Therefore, it is not known whether propoxyphene can affect reproduction or cause fetal harm when administered to a pregnant woman. Propoxyphene should be given to a pregnant woman only if clearly needed.

Clinical Considerations

Propoxyphene and its major metabolite, norpropoxyphene, cross the human placenta. Neonates whose mothers have taken opiates chronically may exhibit respiratory depression or withdrawal symptoms.

Data

In published animal reproduction studies, no teratogenic effects occurred in offspring born to pregnant rats or rabbits that received propoxyphene during organogenesis. Pregnant animals received propoxyphene doses approximately 10-fold (rats) and 4-fold (rabbits) the maximum recommended human dose (based on mg/m^2 body surface area comparison).

Nursing Mothers

Propoxyphene, norpropoxyphene (major metabolite), are excreted in human milk. Published studies of nursing mothers using propoxyphene detected no adverse effects in nursing infants. Based on a study of six mother-infant pairs, an exclusively breastfed infant receives approximately 2% of the maternal weight-adjusted dose. Norpropoxyphene is renally excreted and renal clearance is lower in neonates than in adults. Therefore, it is possible that prolonged maternal propoxyphene use could result in norpropoxyphene accumulation in a breastfed infant. Watch breast-feeding infants for signs of sedation including poor feeding, somnolence or respiratory depression. Caution should be exercised when propoxyphene is administered to a nursing woman.

Pediatric Use

Safety and effectiveness in pediatric patients have not been established.

Elderly Patients

Clinical studies of propoxyphene did not include sufficient numbers of subjects aged 65 and over to determine whether they respond differently from younger subjects. However, post-marketing reports suggest that patients over the age of 65 may be more susceptible to CNS-related side effects. Therefore, dose selection for an elderly patient should be cautious, usually starting at the low end of the dosing range, reflecting the greater frequency of decreased hepatic, renal or cardiac function, and of concomitant disease or other drug therapy. Decreased total daily dosage should be considered (see DOSAGE AND ADMINISTRATION).

ADVERSE REACTIONS

In hospitalized patients, the most frequently reported were dizziness, sedation, nausea and vomiting. Other adverse reactions include constipation, abdominal pain, skin rashes, lightheadedness, headache, weakness, euphoria, dysphoria, hallucinations and minor visual disturbances.

The most frequently reported post-marketing adverse events have included completed suicide, accidental and intentional overdose, drug dependence, cardiac arrest, coma, drug ineffective, drug toxicity, nausea, respiratory arrest, cardio-respiratory arrest, death, vomiting, dizziness, convulsion, confusional state and diarrhea.

Additional adverse experiences reported through post-marketing surveillance include:

Cardiac Disorders: arrhythmia, bradycardia, cardiac/respiratory arrest, congestive arrest, congestive heart failure (CHF), tachycardia, myocardial infarction (MI)

Eye Disorder: eye swelling, vision blurred

General Disorder and Administration Site Conditions: drug interaction, drug tolerance, drug withdrawal syndrome

Gastrointestinal Disorder: gastrointestinal bleed, acute pancreatitis

Hepatobiliary Disorder: hepatic steatosis, hepatomegaly, hepatocellular injury

Immune System Disorder: hypersensitivity

Injury Poisoning and Procedural Complications: drug toxicity, hip fracture, multiple drug overdose, narcotic overdose

Investigations: blood pressure decreased, heart rate elevated/abnormal

Metabolism and Nutrition Disorder: metabolic acidosis

Nervous System Disorder: ataxia, coma, dizziness, somnolence, syncope

Psychiatric: abnormal behavior, confusional state, hallucinations, mental status change

Respiratory, Thoracic and Mediastinal Disorders: respiratory depression, dyspnoea

Skin and Subcutaneous Tissue Disorder: rash, itch.

Liver dysfunction has been reported in association with propoxyphene. Propoxyphene therapy has been associated with abnormal liver function tests and, more rarely, with instances of reversible jaundice (including cholestatic jaundice).

Subacute painful myopathy has been reported following chronic propoxyphene overdosage.

OVERDOSAGE

Overdose of propoxyphene may present with the signs and symptoms of propoxyphene overdose. Fatalities within the first hour of overdosage are not uncommon.

In all cases of suspected overdosage, call your regional Poison Control Center to obtain the most up-to-date information about the treatment of overdose. This recommendation is made because, in general, information regarding the treatment of overdosage may change more rapidly than do package inserts.

Initial consideration should be given to the management of the CNS effects of propoxyphene overdosage. Resuscitative measures should be initiated promptly.

Symptoms of Propoxyphene Overdosage

The manifestations of acute overdosage with propoxyphene are those of narcotic overdosage. The patient is usually somnolent but may be stuporous or comatose and convulsing. Respiratory depression is characteristic. The ventilatory rate and/or tidal volume is decreased, which results in cyanosis and hypoxia. Pupils, initially pinpoint, may become dilated as hypoxia increases. Cheyne-Stokes respiration and apnea may occur. Blood pressure and heart rate are usually normal initially, but blood pressure falls and cardiac performance deteriorates, which ultimately results in pulmonary edema and circulatory collapse, unless the respiratory depression is corrected and adequate ventilation is restored promptly. Cardiac arrhythmias and conduction delay may be present. A combined respiratory-metabolic acidosis occurs owing to retained CO2 (hypercapnia) and to lactic acid formed during anaerobic glycolysis. Acidosis may be severe if large amounts of salicylates have also been ingested. Death may occur.

Treatment of Propoxyphene Overdosage

Attention should be directed first to establishing a patent airway and to restoring ventilation. Mechanically assisted ventilation, with or without oxygen, may be required, and positive pressure respiration may be desirable if pulmonary edema is present. The opioid antagonist naloxone will markedly reduce the degree of respiratory depression, and should be administered promptly, preferably intravenously. The duration of action of the antagonist may be brief. If no response is observed after 10 mg of naloxone have been administered, the diagnosis of propoxyphene toxicity should be questioned.

In addition to the use of an opioid antagonist, the patient may require careful titration with an anticonvulsant to control convulsions. Activated charcoal can adsorb a significant amount of ingested propoxyphene. Dialysis is of little value in poisoning due to propoxyphene. Efforts should be made to determine whether other agents, such as alcohol, barbiturates, tranquilizers or other CNS depressants, were also ingested, since these increase CNS depression as well as cause specific toxic effects or death.

DOSAGE AND ADMINISTRATION

Propoxyphene hydrochloride capsules are intended for the management of mild to moderate pain. The dose should be individually adjusted according to severity of pain, patient response and patient size.

Propoxyphene hydrochloride capsules are given orally. The usual dosage is one 65 mg propoxyphene hydrochloride capsule every 4 hours as needed for pain. The maximum dose of propoxyphene hydrochloride capsules is 6 capsules per day. Do not exceed the maximum daily dose.

Patients receiving propoxyphene and any CYP3A4 inhibitor should be carefully monitored for an extended period of time and dosage adjustments should be made if warranted.

Consideration should be given to a reduced total daily dosage in elderly patients and in patients with hepatic or renal impairment.

Cessation of Therapy

For patients who used propoxyphene hydrochloride capsules on a regular basis for a period of time, when therapy with propoxyphene hydrochloride capsules is no longer needed for the treatment of their pain, it may be useful to gradually discontinue the propoxyphene hydrochloride capsules over time to prevent the development of an opioid abstinence syndrome (narcotic withdrawal). In general, therapy can be decreased by 25% to 50% per day with careful monitoring for signs and symptoms of withdrawal (see DRUG ABUSE AND DEPENDENCE for description of the signs and symptoms of withdrawal). If the patient develops these signs or symptoms, the dose should be raised to the previous level and titrated down more slowly, either by increasing the interval between decreases, decreasing the amount of change in dose, or both.

HOW SUPPLIED

Propoxyphene Hydrochloride Capsules, USP are available containing 65 mg of propoxyphene hydrochloride, USP.

The 65 mg capsule is a hard-shell hypromellose capsule with a rose opaque cap and a rose opaque body, axially printed with MYLAN over 7065 in black ink on both the cap and the body. The capsule is filled with white to off-white powder. They are available as follows:

NDC 0378-7065-01
bottles of 100 capsules

NDC 0378-7065-05
bottles of 500 capsules

Store at 20º to 25ºC (68º to 77ºF). [See USP Controlled Room Temperature.]

Dispense in a tight, light-resistant container as defined in the USP using a child-resistant closure.

WARNINGS

- There have been numerous cases of accidental and intentional overdose with propoxyphene products either alone or in combination with other CNS depressants, including alcohol. Fatalities within the first hour of overdosage are not uncommon. Many of the propoxyphene-related deaths have occurred in patients with previous histories of emotional disturbances or suicidal ideation/attempts and/or concomitant administration of sedatives, tranquilizers, muscle relaxants, antidepressants or other CNS-depressant drugs. Do not prescribe propoxyphene for patients who are suicidal or have a history of suicidal ideation.
- The metabolism of propoxyphene may be altered by strong CYP3A4 inhibitors (such as ritonavir, ketoconazole, itraconazole, troleandomycin, clarithromycin, nelfinavir, nefazadone, amiodarone, amprenavir, aprepitant, diltiazem, erythromycin, fluconazole, fosamprenavir, grapefruit juice and verapamil) leading to enhanced propoxyphene plasma levels. Patients receiving propoxyphene and any CYP3A4 inhibitor should be carefully monitored for an extended period of time and dosage adjustments should be made if warranted (see CLINICAL PHARMACOLOGY: Drug Interactions and WARNINGS, PRECAUTIONS and DOSAGE AND ADMINISTRATION for further information).

PATIENT COUNSELING INFORMATION

PROPOXYPHENE HYDROCHLORIDE - propoxyphene hydrochloride capsule
Mylan Pharmaceuticals Inc.

----------

MEDICATION GUIDE
PROPOXYPHENE HYDROCHLORIDE CAPSULES, USP

Read this Medication Guide before you start taking propoxyphene hydrochloride capsules, and each time you get a refill. There may be new information. This information does not take the place of talking to your doctor about your medical condition or your treatment.

What is the most important information I should know about propoxyphene hydrochloride capsules?

Propoxyphene hydrochloride capsules and other medicines that contain propoxyphene can cause serious side effects, including:

Overdoses by accident or on purpose (intentional overdose). Overdoses with propoxyphene hydrochloride capsules may happen when it is taken by itself, or with alcohol or other medicines that can also decrease your breathing and make you very sleepy.

- Death can happen within 1 hour of taking an overdose of propoxyphene hydrochloride capsules.
  Many of the deaths that happen in people who take propoxyphene hydrochloride capsules happen in those who:
  - have emotional problems
  - have thoughts of suicide or attempted suicide, or
  - also take antidepressants, sedatives, tranquilizers, muscle relaxants or other medicines that affect your breathing and make you very sleepy. You should not use any of these medicines with propoxyphene hydrochloride capsules without talking to your doctor.
- Before taking propoxyphene hydrochloride capsules tell your doctor if you:
  - have a lung problem, such as COPD or cor pulmonale
  - have liver or kidney problems
  - have problems with your pancreas or gallbladder
  - have a history of head injury
  - are over age 65
  - have a history of drug or alcohol abuse or addiction

Take propoxyphene hydrochloride capsules exactly as prescribed. Do not change your dose or stop taking propoxyphene hydrochloride capsules without first talking to your doctor.

- If you take propoxyphene hydrochloride capsules, do not take more than 6 capsules in one day.
- Before taking propoxyphene hydrochloride capsules, tell your doctor about all the medicines you take. Propoxyphene hydrochloride capsules and many other medicines may interact with each other and may cause serious side effects. Certain medicines can affect how your liver breaks down other medicines. See “What should I tell my doctor before taking propoxyphene hydrochloride capsules?”
- Do not drink grapefruit juice or eat grapefruit while you take propoxyphene hydrochloride capsules. Grapefruit juice may interact with propoxyphene hydrochloride capsules.
- Do not drink alcohol while using propoxyphene hydrochloride capsules. Using alcohol with propoxyphene hydrochloride capsules may increase your risk of having dangerous side effects.

What are propoxyphene hydrochloride capsules?

- Propoxyphene hydrochloride capsules are a prescription medicine used to treat mild to moderate pain.

- Propoxyphene hydrochloride capsules are a federally controlled substance (C-IV) because they are strong opioid pain medicines that can be abused by people who abuse prescription medicines or street drugs.
- Prevent theft, misuse or abuse. Keep propoxyphene hydrochloride capsules in a safe place to protect it from being stolen. Propoxyphene hydrochloride capsules can be a target for people who misuse or abuse prescription medicines or street drugs.
- Never give propoxyphene hydrochloride capsules to anyone else, even if they have the same symptoms that you have. It may harm them or even cause death. Selling or giving away this medicine is against the law.

It is not known if propoxyphene hydrochloride capsules are safe and effective in children younger than age 18.

Who should not take propoxyphene hydrochloride capsules?

Do not take propoxyphene hydrochloride capsules if you:

- are allergic to propoxyphene. Ask your doctor if you are not sure. See the end of this Medication Guide for a list of the ingredients in propoxyphene hydrochloride capsules.
- are having an asthma attack or have severe asthma, trouble breathing or have a lung problem
- have a bowel blockage called paralytic ileus

What should I tell my doctor before taking propoxyphene hydrochloride capsules?

Before you take propoxyphene hydrochloride capsules, tell your doctor:

- if you have any of the conditions listed in the section “What is the most important information I should know about propoxyphene hydrochloride capsules?”
- if you are allergic to propoxyphene
- if you plan to have surgery with general anesthesia
- if you are pregnant or plan to become pregnant.
- if you take propoxyphene hydrochloride capsules regularly before your baby is born, your newborn baby may have withdrawal symptoms because their body has become used to the medicine. Symptoms of withdrawal in a newborn baby may include:
  - irritability
  - shaking (tremors)
  - jitteriness
  - breathing faster than normal
  - crying more than usual
  - diarrhea or more stools than normal
  - vomiting
  - fever
- if you take propoxyphene hydrochloride capsules right before your baby is born, your baby could have breathing problems.
- if you are breast-feeding or plan to breast-feed. Some propoxyphene hydrochloride capsules passes into breast milk.

Tell your doctor about all the medicines you take, including prescription, and nonprescription medicines, vitamins and herbal supplements. Propoxyphene hydrochloride capsules interact with many medicines and may lead to serious side effects. The doses of certain medicines may need to be changed.

Especially tell your doctor if you take:

See “What is the most important information I should know about propoxyphene hydrochloride capsules?”

- certain medicines that can affect how your liver breaks down other medicines
- a monoamine oxidase inhibitor (MAOI) medicine
- other medicines that make you sleepy, such as: other medicines for pain, including other opioid medicines, antidepressant medicines, sleeping pills, anti-anxiety medicines, muscle relaxants, anti-nausea medicines or tranquilizers
- a blood pressure medicine
- a blood-thinner medicine. You may have an increased risk of bleeding while also taking propoxyphene hydrochloride capsules.

Ask your doctor or pharmacist if you are not sure if your medicine is one listed above.

Know the medicines you take. Keep a list of them to show to your doctor and pharmacist when you get a new medicine.

How should I take propoxyphene hydrochloride capsules?

See “What is the most important information I should know about propoxyphene hydrochloride capsules?”

- Take propoxyphene hydrochloride capsules exactly as prescribed.
- If you take too much propoxyphene hydrochloride capsules, or take it with alcohol or other medicines, you may overdose. See “What is the most important information I should know about propoxyphene hydrochloride capsules?” You will need medical help right away if you think you have taken an overdose of propoxyphene hydrochloride capsules. A large overdose could cause you to become unconscious and die.

Signs and symptoms of an overdose of propoxyphene hydrochloride capsules include:

- you are very sleepy or do not respond to others
- confusion
- have trouble breathing or stop breathing
- changes in blood pressure and heart rate

What are the possible side effects of propoxyphene hydrochloride capsules?

Propoxyphene hydrochloride capsules can cause serious side effects, including:

See “What is the most important information I should know about propoxyphene hydrochloride capsules?”

- Serious breathing problems that can become life threatening. This is especially true if you already have a serious lung or breathing problem, or your body is not used to opioid pain medicines. This can happen even if you take propoxyphene hydrochloride capsules exactly as prescribed by your doctor. Call your doctor or get medical help right away if:
  - your breathing slows down
  - you have shallow breathing (little chest movement with breathing)
  - you feel faint, dizzy, confused, or
  - you have any other unusual symptoms
- Propoxyphene hydrochloride capsules can cause your blood pressure to drop. This can make you feel dizzy and faint if you get up too fast from sitting or lying down. Low blood pressure is also more likely to happen if you take other medicines that can also lower your blood pressure. Severe low blood pressure can happen if you lose blood or take certain other medicines.
- Sleepiness. Propoxyphene hydrochloride capsules can cause sleepiness and may affect your ability to make decisions, think clearly, or react quickly. Do not drive, operate heavy machinery, or do other dangerous activities until you know how propoxyphene hydrochloride capsules affects you.
- Propoxyphene hydrochloride capsules can cause physical dependence if you take it for more than a few weeks. Do not stop taking propoxyphene hydrochloride capsules all of a sudden. You could become sick with uncomfortable withdrawal symptoms (for example, nausea, vomiting, diarrhea, anxiety and shivering) because your body has become used to the medicine. Physical dependence is not the same as drug addiction. Your doctor can tell you more about the differences between physical dependence and drug addiction.
  Tell your doctor if you have any of these withdrawal symptoms while you slowly stop taking propoxyphene hydrochloride capsules. You may need to stop propoxyphene hydrochloride capsules more slowly.

Common side effects of propoxyphene hydrochloride capsules include:

- dizziness
- feeling sleepy
- nausea and vomiting
- constipation
- stomach area (abdominal) pain
- skin rashes
- lightheadedness
- headache
- weakness
- feeling of excitement (elation) or discomfort
- seeing, hearing or sensing things that are not really there (hallucinations)
- blurred vision

Call your doctor for medical advice about side effects. You may report side effects to FDA at 1-800-FDA-1088.

You may also report side effects to Mylan Pharmaceuticals, Inc. at 1-877-446-3679 (1-877-4-INFO-RX).

How should I store propoxyphene hydrochloride capsules?

- Store propoxyphene hydrochloride capsules at 20oC to 25oC (68oF to 77oF).

Keep propoxyphene hydrochloride capsules and all medicines out of the reach of children.

General information about propoxyphene hydrochloride capsules

Medicines are sometimes prescribed for purposes other than those listed in a Medication Guide. Do not use propoxyphene hydrochloride capsules for a purpose for which it was not prescribed. Do not give propoxyphene hydrochloride capsules to others even if they have the same symptoms you have. It may harm them and is against the law.

This Medication Guide summarizes the most important information about propoxyphene hydrochloride capsules. If you would like more information, talk with your doctor. You can ask your pharmacist or doctor for information about propoxyphene hydrochloride capsules that is written for health professionals. For more information, call Mylan Pharmaceuticals, Inc. at 1-877-446-3679 (1-877-4-INFO-RX).

What are the ingredients in propoxyphene hydrochloride capsules, USP?

Active ingredient: propoxyphene hydrochloride, USP

Inactive ingredients: anhydrous lactose, magnesium stearate, microcrystalline cellulose, pregelatinized starch and sodium lauryl sulfate. The empty hard-shell hypromellose capsule shells contain carnauba wax, carrageenan, hypromellose, potassium chloride, synthetic red iron oxide and titanium dioxide. In addition, the imprinting ink contains black iron oxide, potassium hydroxide, propylene glycol, shellac and strong ammonia solution.

This Medication Guide has been approved by the U.S. Food and Drug Administration.

Mylan Pharmaceuticals Inc.
Morgantown, WV 26505

OCTOBER 2009
MG:PHCL:R1

Revised: 10/2009 Mylan Pharmaceuticals Inc.

PACKAGE LABEL

propoxyphene65mg